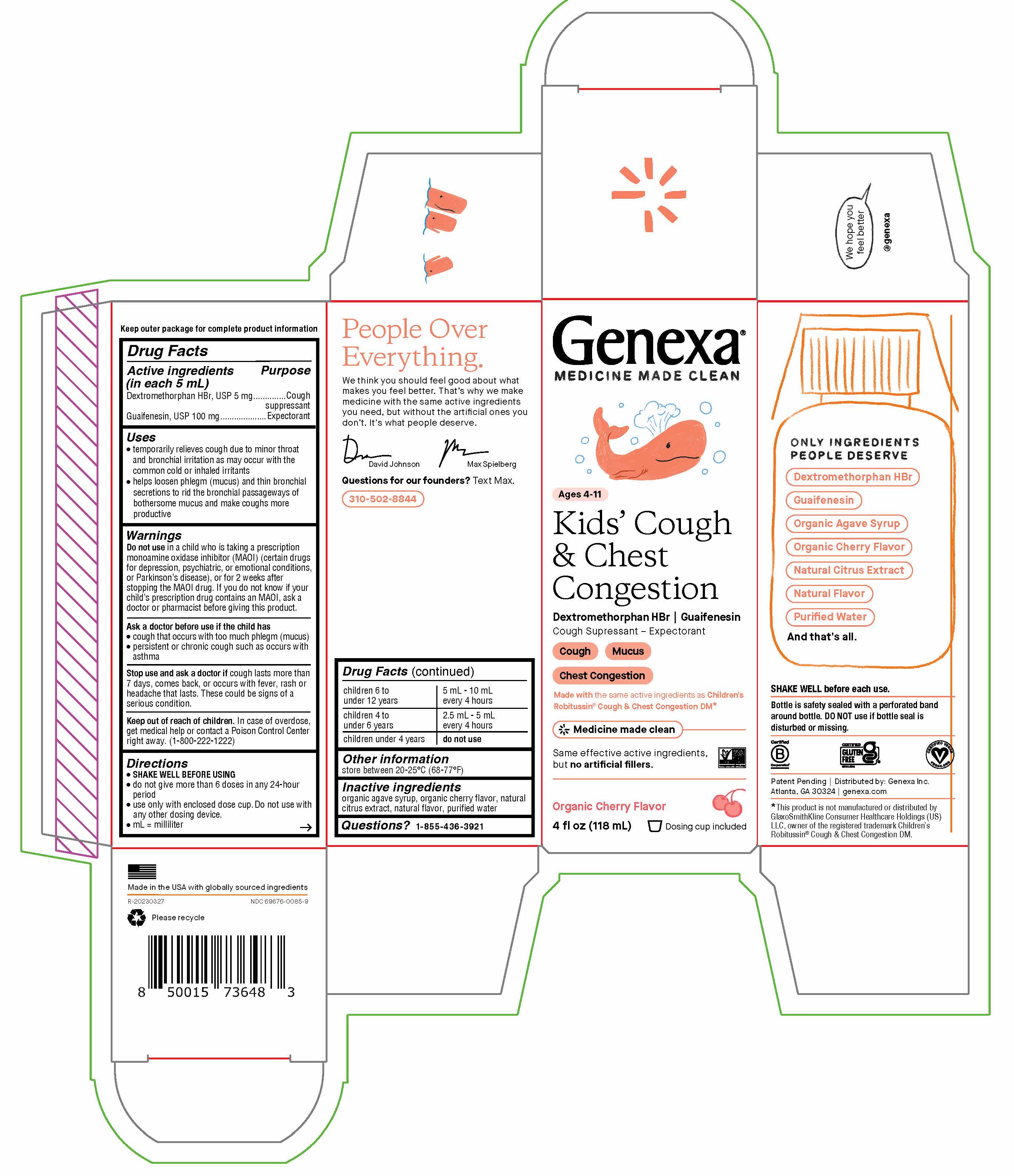 DRUG LABEL: Kids Cough and Chest Congestion
NDC: 69676-0085 | Form: SOLUTION
Manufacturer: Genexa Inc.
Category: otc | Type: HUMAN OTC DRUG LABEL
Date: 20230815

ACTIVE INGREDIENTS: GUAIFENESIN 100 mg/5 mL; DEXTROMETHORPHAN HYDROBROMIDE 5 mg/5 mL
INACTIVE INGREDIENTS: AGAVE TEQUILANA STEM; WATER; CITRUS FRUIT

Kids' Cough & Chest Congestion Organic Cherry Flavor

Drug Facts

Active ingredients (in each 5 mL)

Dextromethorphan HBr, USP 5 mg

Guaifenesin, USP 100 mg

Purposes

Cough suppressant

Expectorant

Uses

- temporarily relieves cough due to minor throat and bronchial irritation as may occur with the common cold or inhaled irritants
- helps loosen phlegm (mucus) and thin bronchial secretions to rid the bronchial passageways of bothersome mucus and make coughs more productive

Warnings

Do not use in a child who is taking a prescription monoamine oxidase inhibitor (MAOI) (certain drugs for depression, psychiatric, or emotional conditions, or Parkinson’s disease), or for 2 weeks after stopping the MAOI drug. If you do not know if your child’s prescription drug contains an MAOI, ask a doctor or pharmacist before giving this product.

Ask a doctor before use if the child has

- cough that occurs with too much phlegm (mucus)
- persistent or chronic cough such as occurs with asthma

Stop use and ask a doctor if cough lasts more than 7 days, comes back, or occurs with fever, rash or headache that lasts. These could be signs of a serious condition.

Keep out of reach of children. In case of overdose, get medical help or contact a Poison Control Center right away. (1-800-222-1222)

Directions

SHAKE WELL BEFORE USING

- do not give more than 6 doses in any 24-hour period
- use only with enclosed dose cup. Do not use with any other dosing device.
- mL = milliliter

children 6 to under 12 years | 5 mL - 10 mL every 4 hours
children 4 to under 6 years | 2.5 mL - 5 mL every 4 hours
children under 4 years | do not use

DIRECTIONS

Added "SHAKE WELL BEFORE USING" under Directions

Other information

store between 20-25°C (68-77°F)

INACTIVE INGREDIENT

Inactive ingredientsorganic agave syrup, organic cherry flavor, natural citrus extract, natural flavor, purified water

Questions?

1-855-436-3921

SHAKE WELL before each use.

Bottle is safety sealed with a perforated band around the bottle. DO NOT use if bottle seal is disturbed or missing.

Patent Pending | Distributed by: Genexa Inc.

Atlanta, GA 30068 | genexa.com

*This product is not manufactured or distributed by

GlaxoSmithKline Consumer Healthcare Holdings (US)

LLC, owner of the registered trademark Children’s

Robitussin® Cough & Chest Congestion DM.

Made in the USA with globally sourced ingredients

NDC 69676-0085-9

PACKAGE LABEL

Genexa®

MEDICINE MADE CLEAN

Ages 4-11

Kids' Cough & Chest Congestion

Dextromethorphan HBr | Guaifenesin

Cough Suppressant - Expectorant

Cough

Mucus

Chest Congestion

Made with the same active ingredients as Children’s

Robitussin® Cough & Chest Congestion DM*

Medicine made clean

Same effective active ingredients,

but no artificial fillers.

Organic Cherry Flavor

4 FL OZ (118 mL)

Dosing cup included